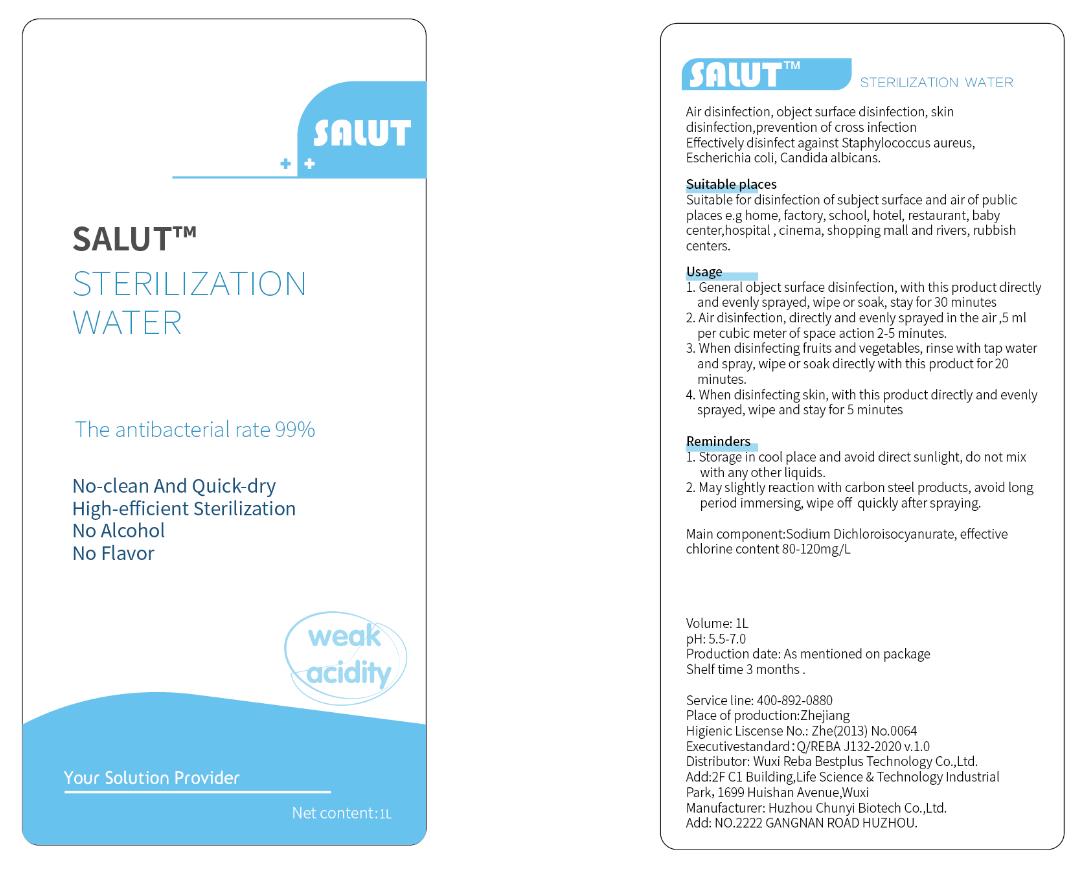 DRUG LABEL: SALUT sterilization water
NDC: 77760-101 | Form: LIQUID
Manufacturer: Wuxi Reba Bestplus Technology Co., Ltd
Category: otc | Type: HUMAN OTC DRUG LABEL
Date: 20200531

ACTIVE INGREDIENTS: TROCLOSENE SODIUM 200 mg/1 L
INACTIVE INGREDIENTS: SODIUM CHLORIDE; WATER; CITRIC ACID MONOHYDRATE; TRISODIUM CITRATE DIHYDRATE

Reba Bestplus, Sterilization water, 1L

Active Ingredient(s)

Sodium dichloroisocyanurate 0.02% w/w. Purpose: Antimicrobial

Purpose

Antimicrobial.

Use

This product is indicated use for disinfection of air, object surface, and skin; prevent of cross infection.

Effectively disinfect against Staphylococcus aureus, Escherichia coli, Candida albicans.

Warnings

External use only.

Do not mix with any other liquids.

Do not use

- on children less than 2 months of age
- on open skin wounds

WHEN USING

When using: avoid direct contact with eyes and damaged skin; if it gets in your eyes accidentally, please rinse with water.

Stop use and ask a doctor if irritation or rash occurs. These may be signs of a serious condition.

KEEP OUT OF REACH OF CHILDREN

This product should be placed out of reach of children.

Directions

1. General object surface disinfection, with this product directly and evenly sprayed, wipe or soak, stay for 30 minutes.

2. Air disinfection, directly and evenly sprayed in the air, 5 ml per cubic meter of space action 2-5 minutes.

3. When disinfecting fruits and vegetables, rinse with tab water and spray, wipe or soak directly with this product for 20 minutes.

4. When disinfecting skin, with this product directly and evenly sprayed, wipe and stay for 5 minutes.

Other information

1. Storage in cool place and avoid directly sunlight, do not mix any other liquids.

2. May slightly reaction with carbon steel products, avoid long period immersing, wipe off quickly after spraying.

Inactive ingredients

Trisodium citrate dihydrate, Citric acid monohydrate, Sodium chloride, Water.